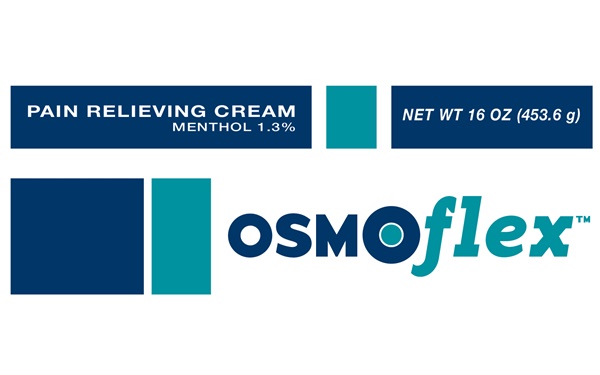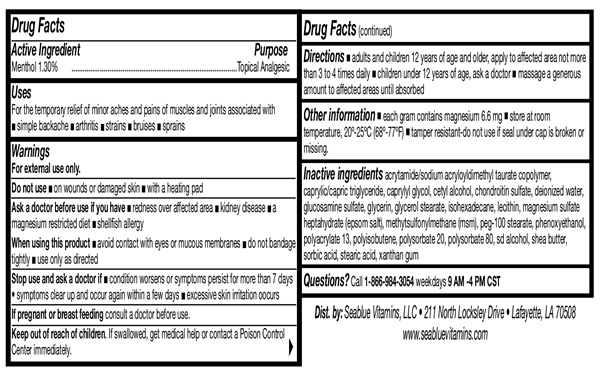 DRUG LABEL: OsmoFlex
NDC: 67676-101 | Form: CREAM
Manufacturer: Sarati International, Inc.
Category: otc | Type: HUMAN OTC DRUG LABEL
Date: 20231027

ACTIVE INGREDIENTS: MENTHOL 1.3 g/100 g
INACTIVE INGREDIENTS: ACRYLAMIDE; TRICAPRYLIN; CAPRYLYL GLYCOL; CETYL ALCOHOL; CHONDROITIN SULFATE (BOVINE); WATER; GLUCOSAMINE SULFATE; GLYCERYL STEARATE CITRATE; ISOHEXADECANE; HYDROGENATED SOYBEAN LECITHIN; MAGNESIUM SULFATE HEPTAHYDRATE; DIMETHYL SULFONE; POLYOXYL 100 STEARATE; PHENOXYETHANOL; POLYISOBUTYLENE (1200000 MW); POLYSORBATE 20; POLYSORBATE 80; ALCOHOL; SHEA BUTTER; SORBIC ACID; STEARIC ACID; XANTHAN GUM

OsmoFlex-101

Drug Facts Active Ingredient

Menthol 1.30%

Purpose

Topical Analgesic

Uses

For the temporary relief of minor aches and pains of muscles and joints associated with

- simple backache
- arthritis
- strains
- bruises
- sprains

Warnings

For External Use Only

Do not use

- on wounds or damaged skin
- with a heating pad

When using this product

- avoid contact with eyes or mucous membranes
- do not bandage tightly
- use only as directed

Stop Use and Ask A Doctor

- if conditions worsen or if symptoms persist for more that 7 days
- symptoms clear up and occur again within a few days
- excessive skin irritation.

If pregnant or breast feedingconsult a doctor before use.

Keep out of reach of children

If swallowed, get medical help or contact a Poison Control Center immediately.

Directions

- adults and children 12 years of age and older, apply to affected area not more than 3 to 4 times daily
- children under 12 years of age, ask a doctor
- massage a generous amount to affected area until absorbed.

Inactive Ingredients

acrylamide/sodium acryloyldimethyl taurate copolymer, caprylic/capric triglyceride, caprylyl glycol, cetyl alcohol, chondroitin sulfate, deionized water, glucosamine sulfate, glycerin, glycerol stearate, isohexadecane, lecithin, magnesium sulfate heptahydrate (epsom salt), methylsulfonylmethane (msm), peg-100, stearate, phenoxyethanol, polyacrylate 13, polyisobutene, polysorbate 20, polysorbate 80, sd alcohol, shea butter, sorbic acid, stearic acid, xanthan gum

Questions

Call 1-866-984-3054

Other Information

- each gram contains magnesium 6.6 mg
- store and use at room temperature 20°-25° C (68°-77° F)
- tamper resistant-do not use if seal under cap is broken or missing.

OsmoFlex product label

OsmoFlex ™

Pain Relieving Cream Menthol 1.3%

Net Wt 4 oz (113.4g)

NET WT 16 OZ (453.6 g)

NET WT 32 OZ (964.3 g)

Dist. by: Seablue Vitamins, LLC • 211 North Locksley Drive • Lafayette, LA 70508

www.seabluevitamins.com

res